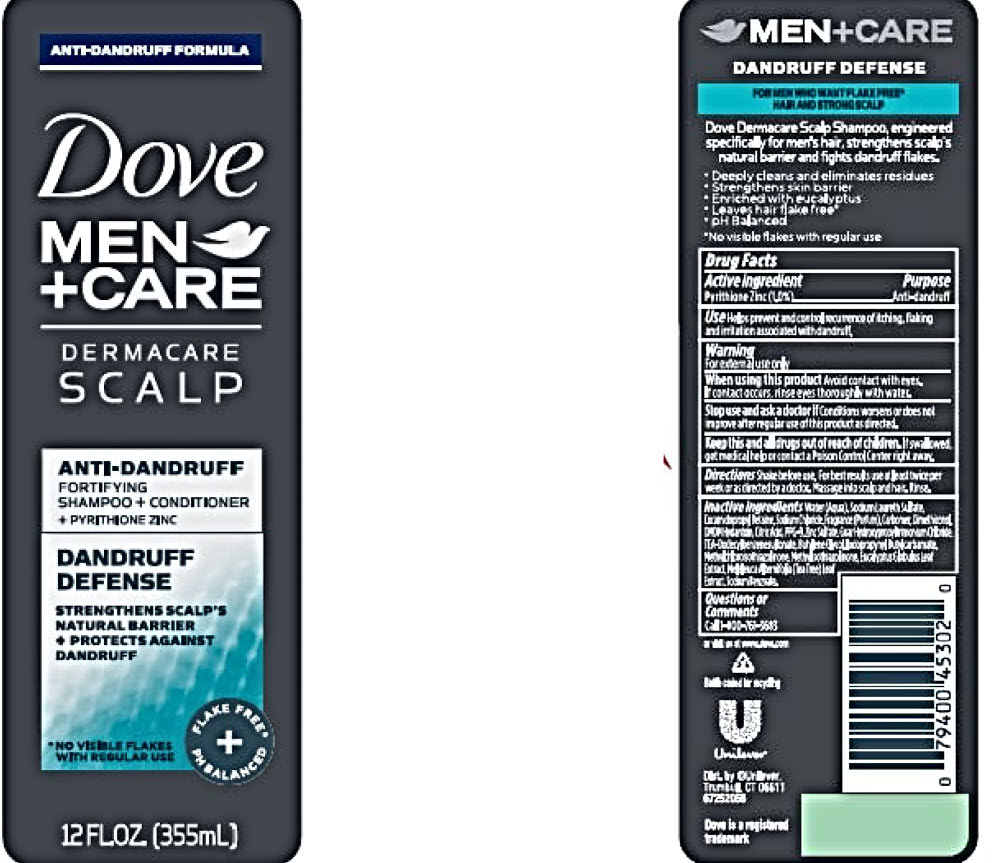 DRUG LABEL: Dove
NDC: 64942-1622 | Form: LIQUID
Manufacturer: Conopco, Inc. d/b/a/ Unilever
Category: otc | Type: HUMAN OTC DRUG LABEL
Date: 20221207

ACTIVE INGREDIENTS: PYRITHIONE ZINC 1 g/100 mL
INACTIVE INGREDIENTS: TEA TREE OIL; EUCALYPTUS OIL; SODIUM BENZOATE; SODIUM CHLORIDE; WATER; SODIUM LAURETH-3 SULFATE; COCAMIDOPROPYL BETAINE; DIMETHICONOL (40 CST); CARBOMER HOMOPOLYMER TYPE C; DMDM HYDANTOIN; GUAR HYDROXYPROPYLTRIMONIUM CHLORIDE (1.7 SUBSTITUENTS PER SACCHARIDE); CITRIC ACID MONOHYDRATE; ZINC SULFATE, UNSPECIFIED FORM; TRIETHANOLAMINE DODECYLBENZENESULFONATE; BUTYLENE GLYCOL; PPG-9; IODOPROPYNYL BUTYLCARBAMATE; METHYLCHLOROISOTHIAZOLINONE; METHYLISOTHIAZOLINONE

Dove Men+Care Dermacare Scalp Dandruff Defense Anti-Dandruff Shampoo + Conditioner

Dove Men+Care Dermacare Scalp Dandruff Defense Anti-Dandruff Shampoo + Conditioner - pyrithione zinc liquid

Dove Men+Care Dermacare Scalp Dandruff Defense Anti-Dandruff Shampoo + Conditioner

Drug Facts

Active ingredient
Pyrithione Zinc (1.0%)

Purpose

Anti-dandruff

Use

• Helps prevent and control recurrence of itching, flaking and irritation associated with dandruff.

Warnings

• For external use only
• When using this product: Avoid contact with eyes. If contact occurs, rinse eyes thoroughtly with water.
• Stop use and ask a doctor if: Condition worsens or does not improve after regular use of this product as directed.

KEEP OUT OF REACH OF CHILDREN

• Keep this and all drugs out of reach of children.
If swallowed, get medical help or contact a Poison Control Center right away.

Directions

For best results use at least twice per week or as directed by a doctor. Massage into scalp and hair. Rinse.

Inactive Ingredients

Water (Aqua), Sodium Laureth Sulfate, Cocamidopropyl Betaine, Sodium Chloride, Fragrance (Parfum), Carbomer, Dimethiconol, DMDM Hydantoin, Citric Acid, PPG-9, Zinc Sulfate, Guar Hydroxypropyltrimonium Chloride, TEA-Dodecylbenzenesulfonate, Butylene Glycol, Iodopropynyl Butylcarbamate, Methylchloroisothiazolinone, Methylisothiazolinone, Eucalyptus Globulus Leaf Extract, Melaleuca Alternifolia (Tea Tree) Leaf Extract, Sodium benzoate.

Questions?

Call 1-800-761-3683